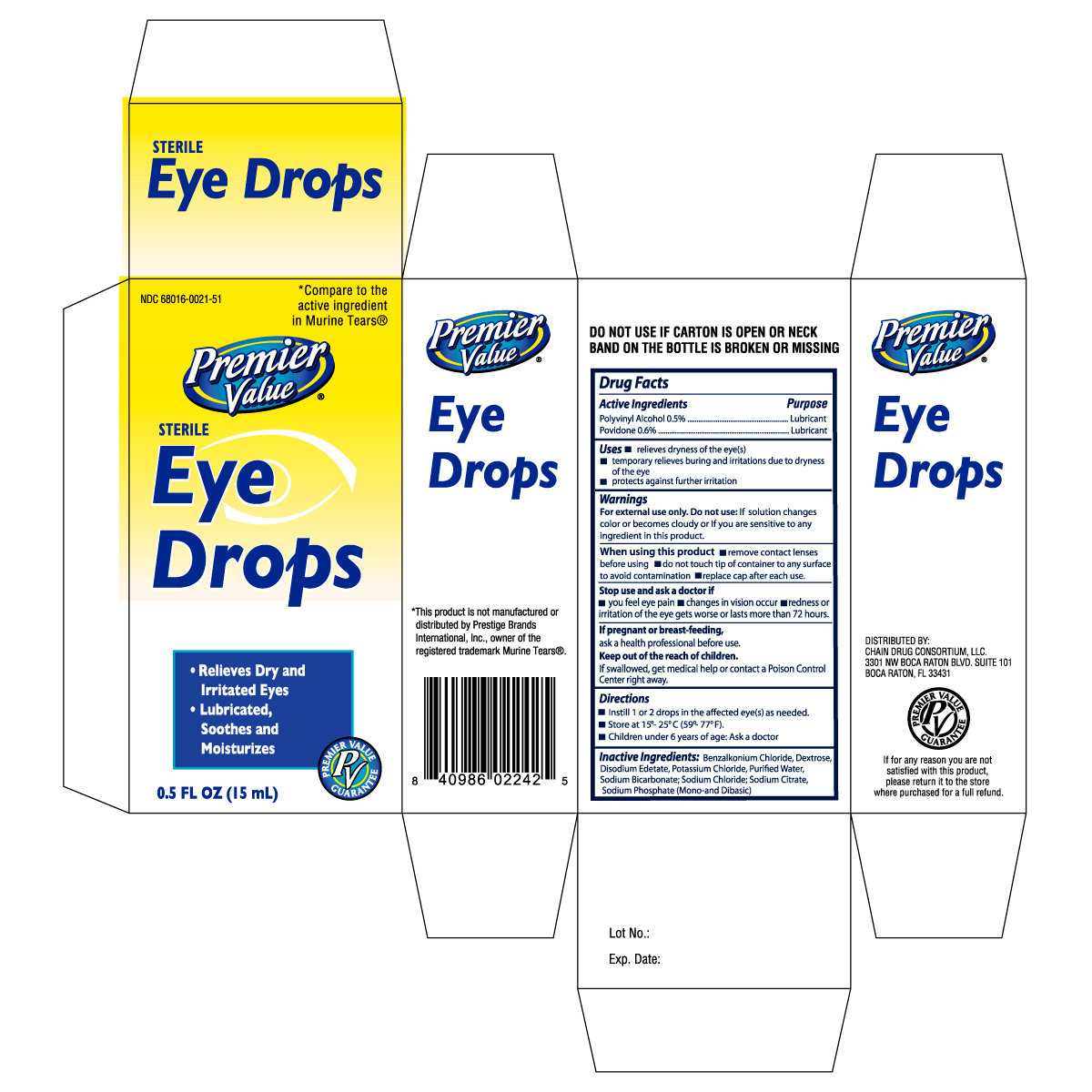 DRUG LABEL: PREMIER VALUE EYE DROPS MT
NDC: 11716-0224 | Form: SOLUTION
Manufacturer: HANLIM PHARM. CO., LTD.
Category: otc | Type: HUMAN OTC DRUG LABEL
Date: 20101019

ACTIVE INGREDIENTS: POLYVINYL ALCOHOL 5 mg/1 mL; POVIDONE 6 mg/1 mL
INACTIVE INGREDIENTS: BENZALKONIUM CHLORIDE; DEXTROSE; EDETATE DISODIUM; POTASSIUM CHLORIDE; WATER; SODIUM BICARBONATE; SODIUM CHLORIDE; SODIUM CITRATE; SODIUM PHOSPHATE

Drug Facts

Active ingredients Purpose

Polyvinyl Alcohol 0.5% ........................................................Lubricant

Povidone 0.6% ...................................................................Lubricant

Uses

- relieves dryness of the eye(s)
- temporary relieves burning and irritations due to dryness of the eye
- protects against further irritation

WARNINGS

For external use only.

Do not use: If solution changes color or becomes cloudy or if you are sensitive to any ingredient in this product.

When using this product

- remove contact lenses before using
- do not touch tip of container to any surface to avoid contamination
- replace cap after each use

Stop use and ask a doctor if

- you feel eye pain
- changes in vision occur
- redness of irritation of the eye gets worse or lasts more than 72 hours

If pregnant or breast-feeding,

ask a health professional before use.

Keep out of the reach of children.

If swallowed, get medical help or contact a Poison Control Center right away.

Directions

- Instill 1 or 2 drops in the affected eye(s) as needed.
- Store at 15o-25oC (59o-77oF).
- Children under 6 years of age: Ask a doctor

INACTIVE INGREDIENT

Inactive Ingredients: Benzalkonium Chloride, Dextrose, Disodium Edetate, Potassium Chloride, Purified Water, Sodium Bicarbonate, Sodium Chloride, Sodium Citrate,

Sodium Phosphate (Mono- and Dibasic)

DOSAGE AND ADMINISTRATION

Distributed By:

Chain Drug Consortium, LLC.

3301 NW Boca Raton Blvd. Suite 101

Boca Raton, FL33431

PACKAGE LABEL

Enter section text here